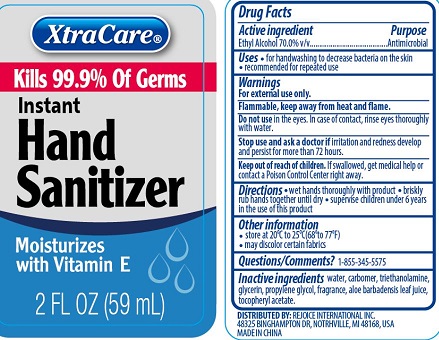 DRUG LABEL: XtraCare Instand Hand Sanitizer
NDC: 58503-090 | Form: LIQUID
Manufacturer: China Ningbo Shangge Cosmetic Technology Corp.
Category: otc | Type: HUMAN OTC DRUG LABEL
Date: 20190918

ACTIVE INGREDIENTS: ALCOHOL 70 g/100 mL
INACTIVE INGREDIENTS: WATER; GLYCERIN; CARBOXYPOLYMETHYLENE; TROLAMINE; PROPYLENE GLYCOL; ALOE VERA LEAF; .ALPHA.-TOCOPHEROL ACETATE

XtraCare Instand Hand Sanitizer

PURPOSE

Antimicrobial

Active Ingredient

Ethyl Alcohol 70%

USAGE

For handwashing to decrease bacteria on the skin. Recommended for repeated use

Directions

Wet hands thoroughly with product

Briskly rub hands together until dry

supervise children under six years in the use of this product

Keep out of reach of children

If swallowed get medical help or contact a poison control center right away.

Avoid contact with eyes. If this occurs, flush thoroughly with water.

Warnings

For external use only

Flammable keep away from heat and flame

Do not use in the eye. in case of contact rinse thoroughly with water.

Stop use and ask doctor if irritation and redness develops and persist for more than 72 hours

INACTIVE INGREDIENT

WATER, CARBOMER, TOCOPHEROL ACETATE, PROPYLENE GLYCOL, ALOE BARBADENSIS LEAF JUICE, TRIETHANOLAMINE, GLYCERIN